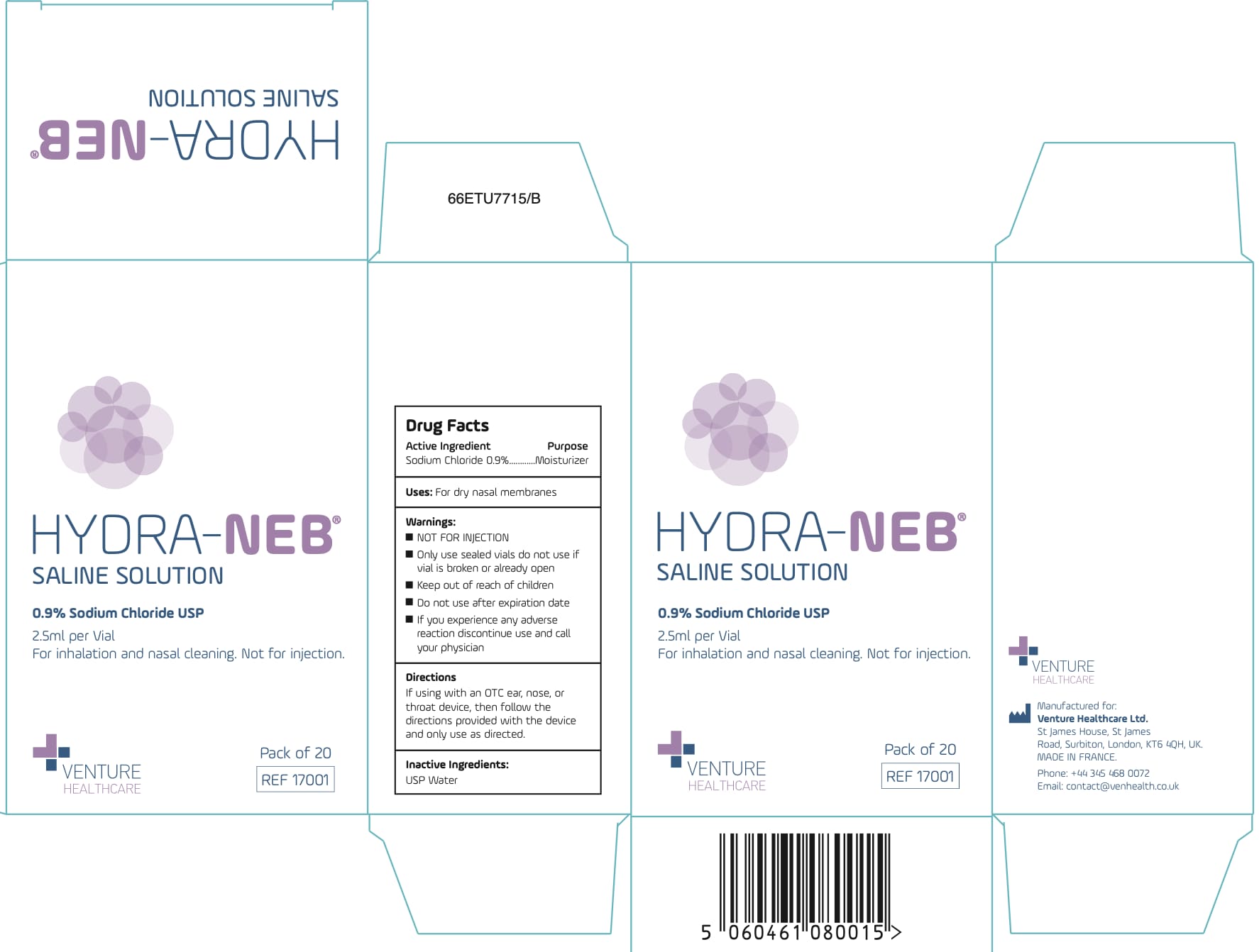 DRUG LABEL: HYDRA NEB
NDC: 43014-1111 | Form: LIQUID
Manufacturer: Laboratoire Unither
Category: otc | Type: HUMAN OTC DRUG LABEL
Date: 20250319

ACTIVE INGREDIENTS: SODIUM CHLORIDE 9 mg/1 mL
INACTIVE INGREDIENTS: WATER

Unither -VentureSaline Solution 0.9% Sodium Chloride

Active ingredient

Sodium Chloride 0.9%

Purpose

Moisturizer

Uses:

For dry nasal membranes

Warnings

NOT FOR INJECTION

Only use sealed vials do not use if vial is broken or already open

Keep out of reach of children
Do not use after expiration date

If you experience any adverse reaction discontinue use and call your physician

• Do not use

after expiration date

- Discontinue if you experience any adverse reaction and call your physician

Directions

If using with an OTC ear, nose, or throat device, then follow the directions provided with the device and only use as directed.

Inactive ingredients

USP Water

Package Labelling:

2.5 mL NDC: 43014-1111-1